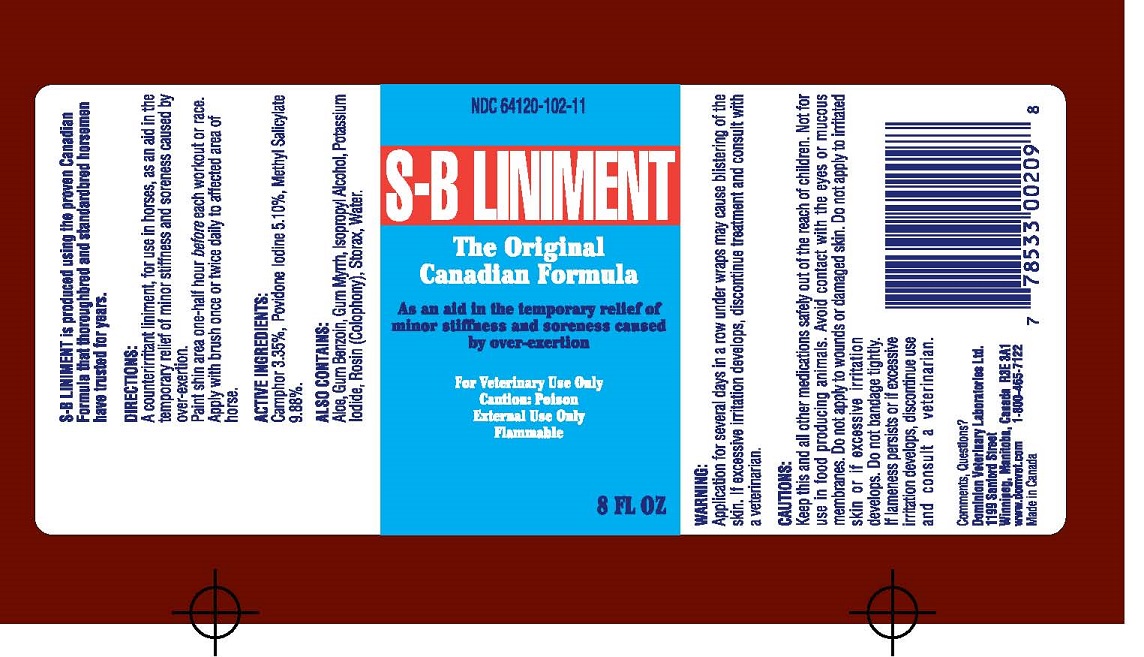 DRUG LABEL: S-B
NDC: 64120-102 | Form: LINIMENT
Manufacturer: DOMINION VETERINARY LABORATORIES LTD.
Category: animal | Type: OTC ANIMAL DRUG LABEL
Date: 20211111

ACTIVE INGREDIENTS: CAMPHOR (NATURAL) 3.35 g/100 mL; POVIDONE-IODINE 5.10 g/100 mL; METHYL SALICYLATE 9.88 g/100 mL
INACTIVE INGREDIENTS: ALOE; BENZOIN RESIN; MYRRH; ISOPROPYL ALCOHOL; POTASSIUM IODIDE; ROSIN; LIQUIDAMBAR ORIENTALIS RESIN

DOMINION VETERINARY LABORATORIES - S-B LINIMENT

ACTIVE INGREDIENTS

CAMPHOR 3.35%

POVIDONE IODINE 5.10%

METHYL SALICYLATE 9.88%

INDICATIONS

FOR USE OF TEMPORARY RELIEF OF MINOR STIFFNESS AND SORENESS.

WARNINGS AND CAUTIONS

WARNINGS

APPLICAATION FOR SEVERAL DAYS IN A ROW UNDER WRAPS MAY CAUSE BLISTERING

OF THE SKIN, iF EXCESSIVE IRRITATION DEVELOPS, DISCONTINUE TREATMENT AND

CONSULT WITH A VETERINARIAN.

DIRECTIONS

A COUNTERIRRITANT LINIMENT, FOR USE IN HORSES, AS AND AID IN THE TEMPORARY

RELIEF OF MINOR STIFFNESS AND SORENESS CAUSED BY OVER-EXERTION.

PAINT SHIN AREA ONE-HALF HOUR BEFORE EACH WORKOUT OR RACE.

APPLY WITH BRUSH ONCE OR TWICE DAILY TO AFFECTED AREA OF HORSE.

KEEP OUT OF REACH OF CHILDREN

KEEP THIS AND ALL OTHER MEDICATIONS SAFELY OUT OF THE REACH OF CHILDREN.

DO NOT USE

NOT FOR USE IN FOOD PRODUCING ANIMALS.

AVOID CONTACT WITH THE EYES OR MUCOUS MEMBRANES.

DO NOT APPLY TO WOUNDS OR DAMAGED SKIN.

DO NOT APPLY TO IRRITATED SKIN OR IF EXESSIVE IRRITATION DEVELOPS.

DO NOT BANDAGE TIGHTLY.

IF KLAMENESS PERSISTS OR IF EXCESSIVE IRRITATION DEVELOPS, DISCONTINUE

USE AND CONSULT A VETERINARIAN.